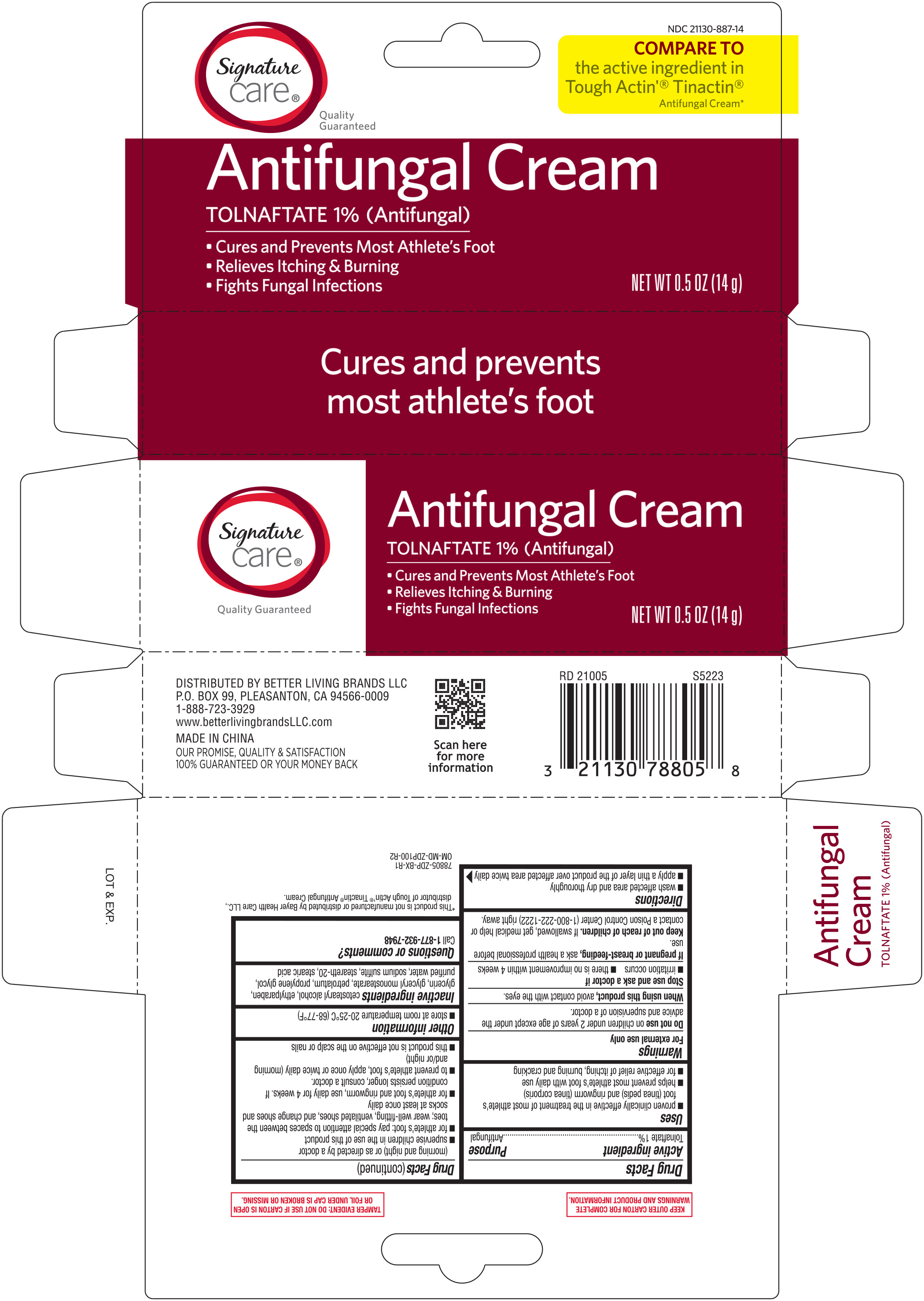 DRUG LABEL: Signature Care Antifungal Cream Tolnaftate 1%
NDC: 21130-887 | Form: CREAM
Manufacturer: BETTER LIVING BRANDS LLC
Category: otc | Type: HUMAN OTC DRUG LABEL
Date: 20251024

ACTIVE INGREDIENTS: TOLNAFTATE 10 mg/1 g
INACTIVE INGREDIENTS: STEARIC ACID; GLYCERIN; PROPYLENE GLYCOL; GLYCERYL MONOSTEARATE; PETROLATUM; WATER; CETOSTEARYL ALCOHOL; STEARETH-20; SODIUM SULFITE; ETHYLPARABEN

Signature Care Antifungal Cream 0.5 oz Tolnaftate 1% 78805 (2021) ZDP

Active ingredient Purpose

Tolnaftate 1%.............................................................Antifungal

Uses

- proven clinically effective in the treatment of most athlete's foot (tinea pedis) and ringworm (tinea corporis)
- helps prevent most athlete's foot with daily use
- for effective relief of itching, burning and cracking

Warnings

For external use only

Do not use on children under 2 years of age, except under the advice and supervision of a doctor.

When using this product, avoid contact with the eyes

Stop use and ask a doctor if

- irritation occurs
- there is no improvement within 4 weeks

Stop use and ask a doctor if

- irritation occurs
- there is no improvement within 4 weeks

PREGNANCY OR BREAST FEEDING

If pregnant or breast-feeding, ask a health professional before use.

Keep out of reach of children. If swallowed, get medical help or contact a Poison Control Center (1-800-222-1222) right away.

Directions

- wash affected area and dry thoroughly
- apply a thin layer of the product over affected area twice daily (morning and night) or as directed by a doctor
- supervise children in the use of this product
- for athlete's foot: pay special attention to spaces between the toes; wear well-fitting, ventilated shoes, and change shoes and socks at least once daily
- for athlete's foot and ringworm, use daily for 4 weeks. If conditions persists longer, consult a doctor.
- to prevent athlete's foot, apply once or twice daily (morning and/or night)
- this product is not effective on the scalp or nails

INACTIVE INGREDIENT

Inactive ingredients cetostearyl alcohol, ethylparaben, glycerin, glyceryl, monostearate, petrolatum, propylene glycol, purified water, sodium sulfite, steareth-20, stearic acid

DOSAGE AND ADMINISTRATION

Distributed by Better Living Brands LLC

P.O. Box 99, Pleasanton, CA 94566

1-888-723-3929

Made in China